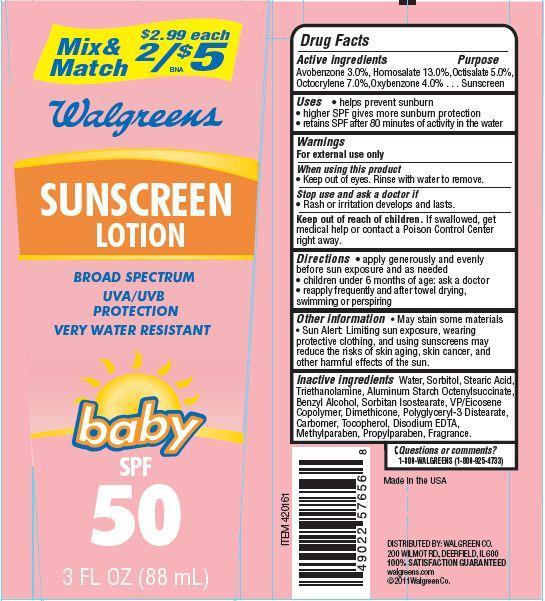 DRUG LABEL: Walgreens Sunscreen Baby
NDC: 0363-4010 | Form: LOTION
Manufacturer: WALGREEN CO.
Category: otc | Type: HUMAN OTC DRUG LABEL
Date: 20121204

ACTIVE INGREDIENTS: HOMOSALATE 13 g/100 g; OXYBENZONE 4 g/100 g; AVOBENZONE 3 g/100 g; OCTISALATE 5 g/100 g; OCTOCRYLENE 7 g/100 g
INACTIVE INGREDIENTS: WATER; SORBITOL; STEARIC ACID; TROLAMINE; ALUMINUM STARCH OCTENYLSUCCINATE; BENZYL ALCOHOL; SORBITAN ISOSTEARATE; DIMETHICONE; TOCOPHEROL; EDETATE DISODIUM; METHYLPARABEN; PROPYLPARABEN

Drug Facts

Active Ingredients

Avobenzone 3.0% Homosalate 13.0% Octisalate 5.0% Octocrylene 7.0% Oxybenzone 4.0% ........Sunscreen

Warnings

For external use only

When using this product

- Keep out of eyes. Rinse with water to remove

stop use and ask a doctor if

- rash or irritation develops and lasts

keep out of reach of children.

If swallowed get medical help or contact a Poison Control Center right away.

Directions

- apply generously and evenly before sun exposure and as needed
- children under 6 months of age:ask a doctor
- reapply frequently and after towel drying, swimming or perspiring

Uses

- helps prevent sunburn
- higher SPF gives more sunburn protection
- retains SPF after 80 minutes of activity in the water

Questions or comments?

1-801-WALGREENS (1-801-925-4733)

Principal Display Panel

Mix and Match $2.99 each
2/$5
Walgreens
SUNSCREEN
LOTION
BROAD SPECTRUM
UVA/UVB
PROTECTION
VERY WATER RESISTANT
baby
SPF
50
3 FL OZ (88 mL)

Inactive Ingredients

Water, Sorbitol, Stearic Acid, Triethanolamine, Aluminum Starch Octenylsuccinate, Benzyl Alcohol, Sorbitan Isostearate, VP/Eicosene Copolymer, Dimethicone, Polyglyceryl-3 Distearate, Carbomer, Tocopherol, Disodium EDTA, Methylparaben, Propylparaben, Fragrance.